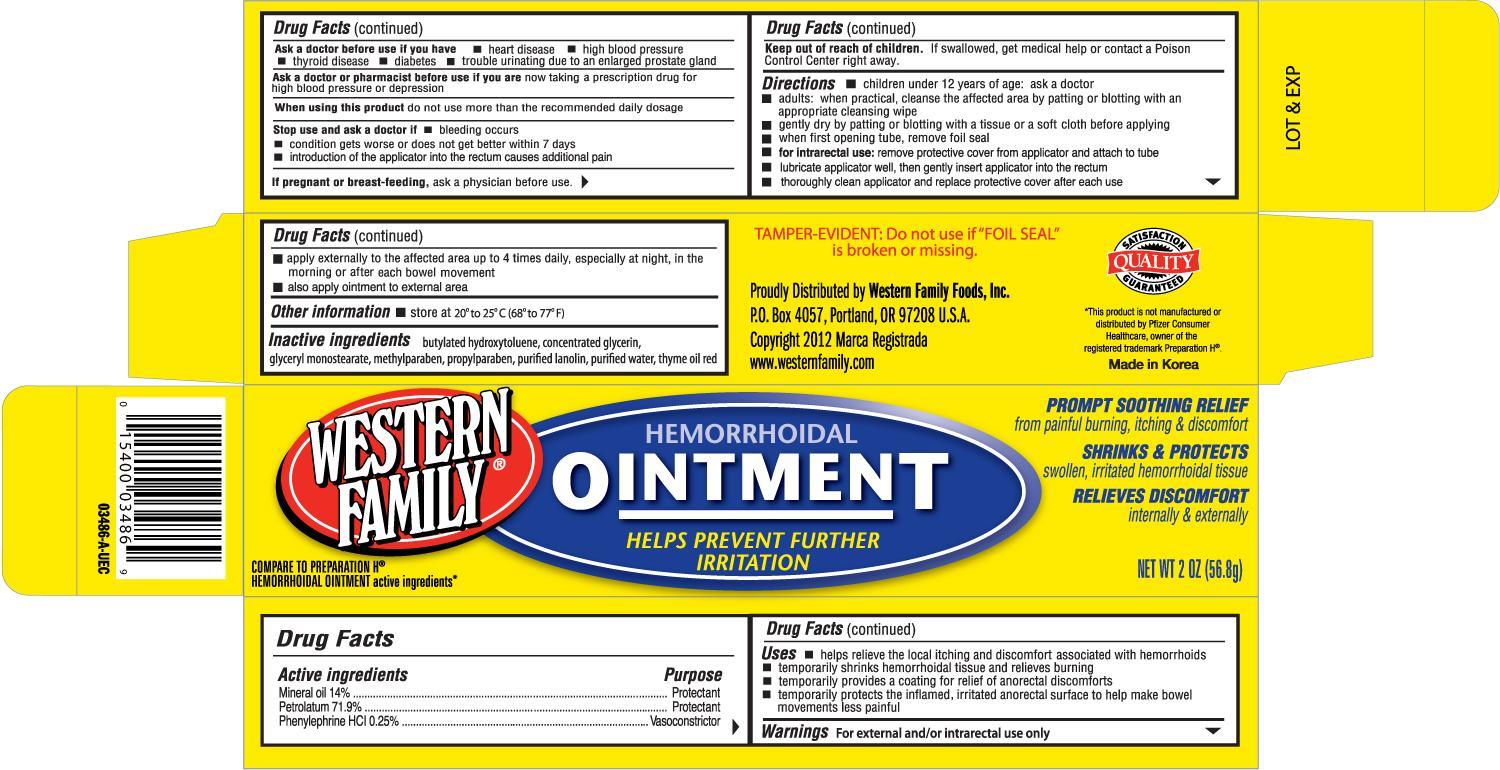 DRUG LABEL: WESTERN FAMILY HEMORRHOIDAL 
NDC: 55312-034 | Form: OINTMENT
Manufacturer: WESTERN FAMILY FOOD, INC.
Category: otc | Type: HUMAN OTC DRUG LABEL
Date: 20120731

ACTIVE INGREDIENTS: MINERAL OIL 140 mg/1 g; PETROLATUM 719 mg/1 g; PHENYLEPHRINE HYDROCHLORIDE 2.5 mg/1 g
INACTIVE INGREDIENTS: BUTYLATED HYDROXYTOLUENE; GLYCERYL MONOSTEARATE; METHYLPARABEN; PROPYLPARABEN; WATER

Drug Facts

Active ingredients Purpose

Mineral oil 14% .................................................................Protectant

Petrolatum 71.9% .............................................................Protectant

Phenylephrine HCL 0.25% .................................................Vasoconstrictor

Uses

- helps relieve the local itching and discomfort associated with hemorrhoids
- temporarily shrinks hemorrhoidal tissue and relieves burning
- temporarily provides a coating for relief of anorectal discomforts
- temporarily protects the inflamed, irritated anorectal surface to help make bowel movements less painful

Warnings

For external and/or intrarectal use only

Ask a doctor before use if you have

- heart disease
- high blood pressure
- thyroid disease
- diabetes
- trouble urinating due to an enlarged prostate gland

Ask a doctor or pharmacist before use if you are now taking a prescription drug for high blood pressure or depression

When using this product do not use more than the recommended daily dosage

Stop use and ask a doctor if

- bleeding occurs
- condition gets worse or does not get better within 7 days
- introduction of the applicator into the rectum causes additional pain

PREGNANCY OR BREAST FEEDING

If pregnant or breast-feeding, ask a physician before use.

Keep out of reach of children.

If swallowed, get medical help or contact a Poison Control Center right away.

Directions

- children under 12 years of age: ask a doctor
- adults: when practical, cleanse the affected area by patting or blotting with an appropriate cleansing wipe
- gently dry by patting or blotting with a tissue or a soft cloth before applying
- when first opening tube, remove foil seal
- for intrarectal use: remove protective cover form applicator and attach to tube
- lubricate applicator well, then gently insert applicator into the rectum
- thoroughly clean applicator and replace protective cover after each use
- apply externally to the affected area up to 4 times daily, especially at night, in the morning or after each bowel movement
- also apply ointment to external area

Other information

Store at 20o to 25oC (68o to 77oF)

Inactive ingredients

benzoic acid, BHA, BHT, methylparaben, paraffin, propylparaben, thyme oil, glyceryl stearate, glycerin, absorb refined lanoline, purified water

DOSAGE AND ADMINISTRATION

Proudly Distributed by Western Family Foods, Inc.

P.O. Box 4057, Portland, OR 97208 USA

www.westernfamily.com

Made in Korea

PACKAGE LABEL

Enter section text here